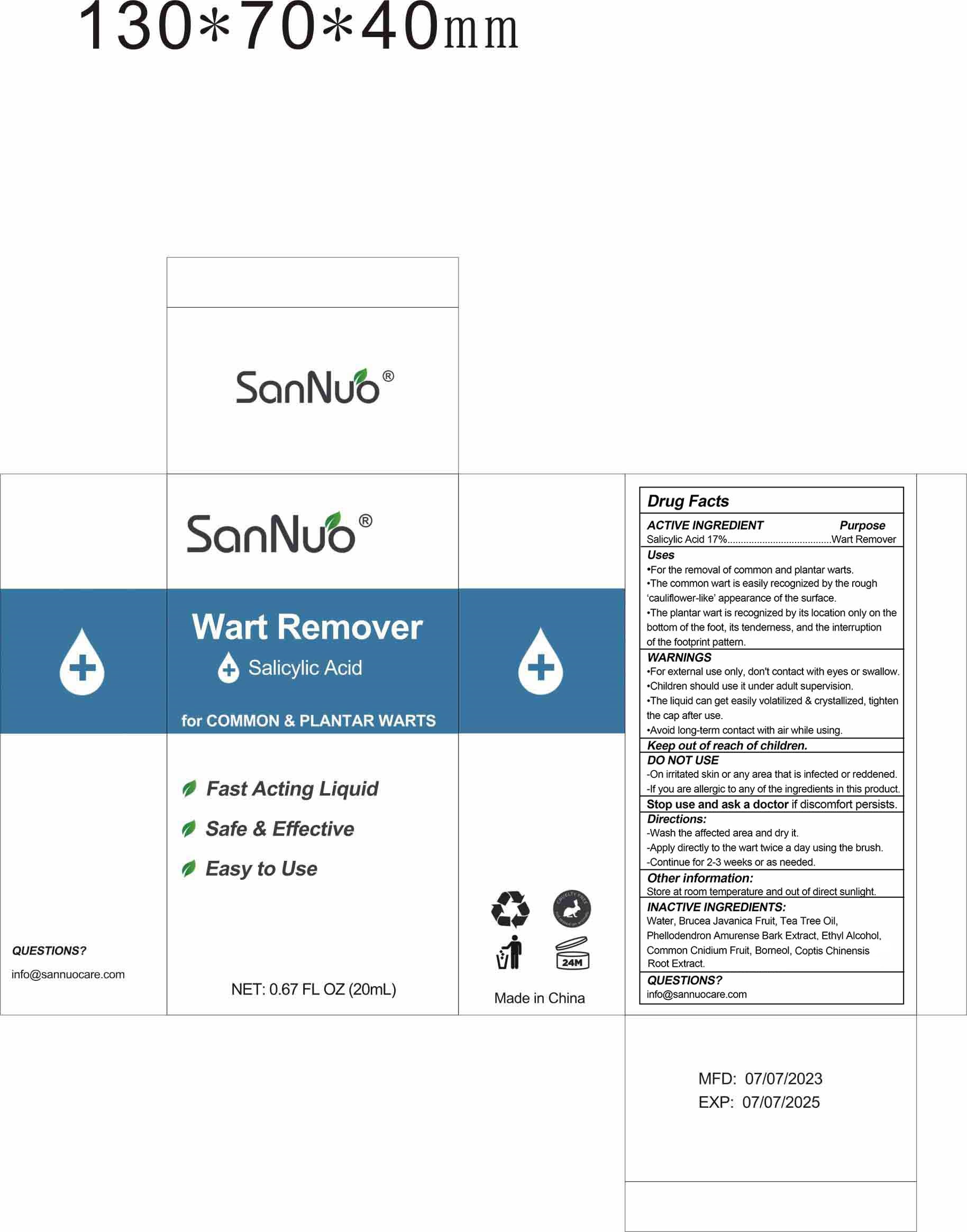 DRUG LABEL: SANNUO WART REMOVER
NDC: 83648-001 | Form: LIQUID
Manufacturer: Shenzhen Baixingchen Technology Co., Ltd.
Category: otc | Type: HUMAN OTC DRUG LABEL
Date: 20230823

ACTIVE INGREDIENTS: SALICYLIC ACID 3.4 g/20 mL
INACTIVE INGREDIENTS: ALCOHOL; WATER; BRUCEA JAVANICA FRUIT; PHELLODENDRON AMURENSE BARK; BORNEOL; COPTIS CHINENSIS ROOT; CNIDIUM MONNIERI FRUIT; TEA TREE OIL

ACTIVE INGREDIENT

Salicylic Acid 17% w/v

DO NOT USE

On irritated skin or any area that is infected or reddened.

If you are allergic to any of the ingredients in this product.

Keep out of reach of children

PURPOSE

Wart Remover

WARNINGS
For external use only,don't contact with eyes or swallow.
Children should use it under adult supervision.
The liquid can get easily volatilized & crystallized,tighten the cap after use.
Avoid long term contact with air while using.

Directions:
Wash the affected area and dry it.
Apply directly to the wart twice a day using the brush.
Continue for 2-3 weeks or as needed.

Uses
For the removal of common and plantar warts
The common wart is easily recognized by the rough cauliflower-like appearance of the surface.
The plantar wart is recognized by its location only on the bottom of the foot, its tenderness, and the interruption of the footprint pattern

INACTIVE INGREDIENTS:

WATER,BRUCEA JAVANICA FRUIT,TEA TREE OIL,PHELLODENDRON AMURENSE BARK EXTRACT, ETHYL ALCOHOL,COMMON CNIDIUM FRUIT, GALLA CHINENSIS, BORNEOL,COPTIS CHINENSIS ROOT EXTRACT.